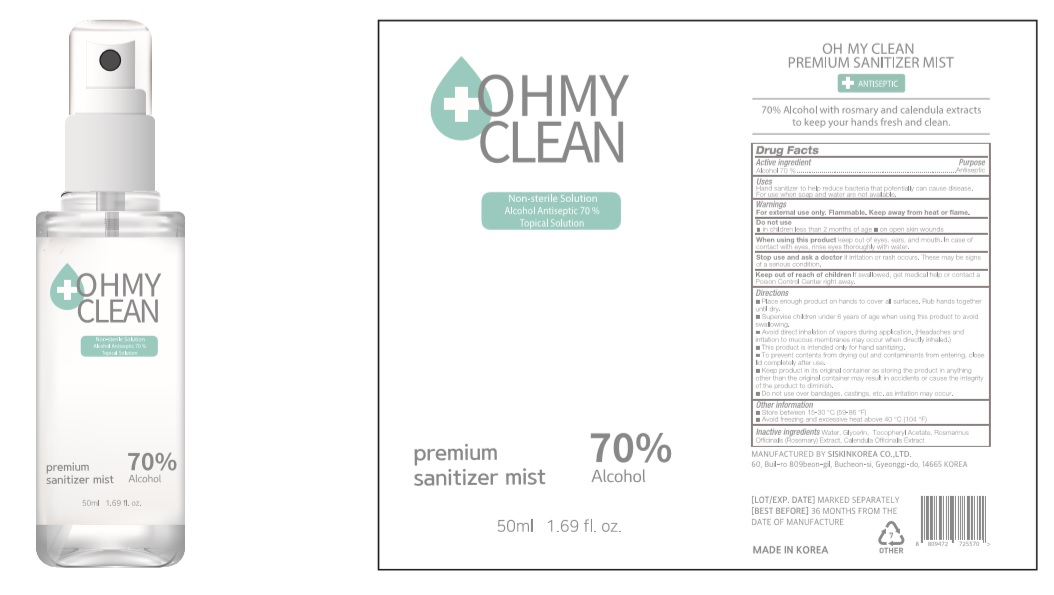 DRUG LABEL: OH MY CLEAN PREMIUM SANITIZER MIST
NDC: 74514-7050 | Form: LIQUID
Manufacturer: SISKINKOREA CO.,LTD.
Category: otc | Type: HUMAN OTC DRUG LABEL
Date: 20200429

ACTIVE INGREDIENTS: ALCOHOL 35 mL/50 mL
INACTIVE INGREDIENTS: GLYCERIN; .ALPHA.-TOCOPHEROL ACETATE; CALENDULA OFFICINALIS WHOLE; WATER; ROSEMARY

OH MY CLEAN PREMIUM SANITIZER MIST [74514-7050-1]